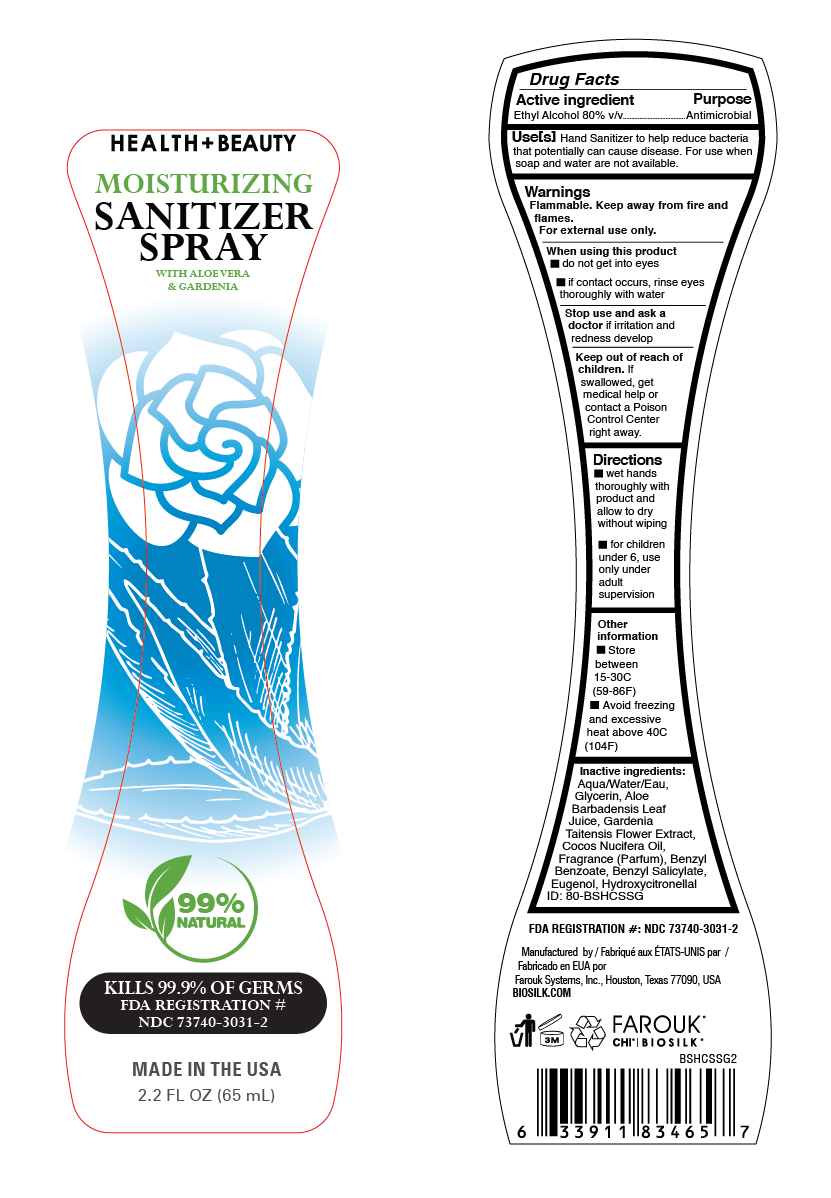 DRUG LABEL: Biosilk Gardenia
NDC: 73740-3031 | Form: SPRAY
Manufacturer: Farouk Systems, Inc.
Category: otc | Type: HUMAN OTC DRUG LABEL
Date: 20201008

ACTIVE INGREDIENTS: ALCOHOL 80 g/100 g
INACTIVE INGREDIENTS: FRAGRANCE FLORAL ORC0902236 0.117225 g/100 g; ALOE VERA LEAF 0.001 g/100 g; BENZYL BENZOATE 0.1295 g/100 g; EUGENOL 0.001075 g/100 g; HYDROXYCITRONELLAL 0.001175 g/100 g; GLYCERIN 2 g/100 g; BENZYL SALICYLATE 0.001025 g/100 g; WATER 22.749 g/100 g

Biosilk Health Beauty Sanitizer Spray Gardenia

Stop use and ask a doctor

Stop use and ask a
doctor if irritation and
redness develop

Active ingredient

Active ingredient Purpose
Ethyl Alcohol 80% v/v Antimicrobial

Stop use and ask a doctor

Stop use and ask a
doctor if irritation and
redness develop

Stop use and ask a doctor

Stop use and ask a
doctor if irritation and
redness develop

Keep out of reach of children.

Keep out of reach of
children. If
swallowed, get
medical help or
contact a Poison
Control Center
right away.

Use[s]

Use[s] Hand Sanitizer to help reduce bacteria
that potentially can cause disease. For use when
soap and water are not available.

Directions

wet hands
thoroughly with
product and
allow to dry
without wiping
for children
under 6, use
only under
adult
supervision

Inactive ingredients:

Aqua/Water/Eau,
Glycerin, Aloe
Barbadensis Leaf
Juice, Gardenia
Taitensis Flower Extract,
Cocos Nucifera Oil,
Fragrance (Parfum), Benzyl
Benzoate, Benzyl Salicylate,
Eugenol, Hydroxycitronellal

Warnings

Flammable. Keep away from fire and
flames.
For external use only.
When using this product
do not get into eyes
if contact occurs, rinse eyes
thoroughly with water
Stop use and ask a
doctor if irritation and
redness develop
Keep out of reach of
children. If
swallowed, get
medical help or
contact a Poison
Control Center
right away.

Use[s]

Use[s] Hand Sanitizer to help reduce bacteria
that potentially can cause disease. For use when
soap and water are not available.

BioSilk Health Beauty Moisturizing Sanitizer Spray with Aloe Vera & Gardenia

99% Natural

Kills 99.9% of Germs

FDA Registration #

NDC 73740-3031-2

Made in the USA

2.2 FL OZ (65 mL)